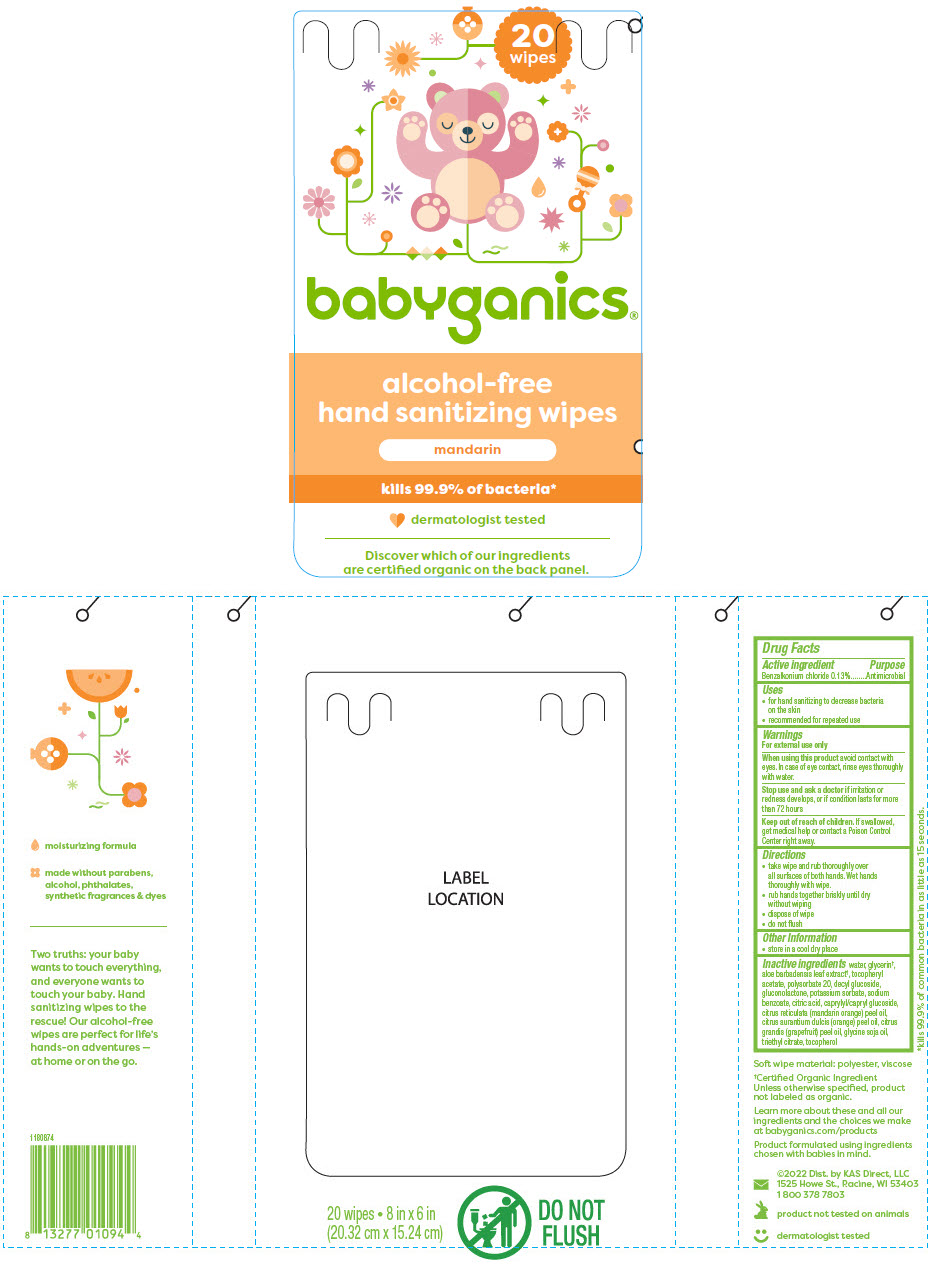 DRUG LABEL: Babyganics Alcohol-Free Hand Sanitizer Wipes Mandarin
NDC: 59062-1194 | Form: CLOTH
Manufacturer: KAS Direct, LLC
Category: otc | Type: HUMAN OTC DRUG LABEL
Date: 20251208

ACTIVE INGREDIENTS: BENZALKONIUM CHLORIDE 13 mg/100 mg
INACTIVE INGREDIENTS: WATER; GLUCONOLACTONE; DECYL GLUCOSIDE; GLYCERIN; POLYSORBATE 20; POTASSIUM SORBATE; SODIUM BENZOATE; CITRIC ACID MONOHYDRATE; ALOE VERA LEAF; CAPRYLYL/CAPRYL OLIGOGLUCOSIDE; MANDARIN OIL; ORANGE PEEL; CITRUS MAXIMA FRUIT RIND OIL; SOYBEAN OIL; TRIETHYL CITRATE; TOCOPHEROL; .ALPHA.-TOCOPHEROL ACETATE

Babyganics® Alcohol-Free Hand Sanitizer Wipes Mandarin

Drug Facts

Active ingredient

Benzalkonium chloride 0.13%

Purpose

Antimicrobial

Uses

- for hand sanitizing to decrease bacteria on the skin
- recommended for repeated use

Warnings

For external use only

When using this product avoid contact with eyes. In case of eye contact, rinse eyes thoroughly with water.

Stop use and ask a doctor if irritation or redness develops, or if condition lasts for more than 72 hours

Keep out of reach of children. If swallowed, get medical help or contact a Poison Control Center right away.

Directions

- take wipe and rub thoroughly over all surfaces of both hands. Wet hands thoroughly with wipe.
- rub hands together briskly until dry without wiping
- dispose of wipe
- do not flush

Other Information

- store in a cool dry place

Inactive ingredients

water, glycerin [Certified Organic Ingredient Unless otherwise specified, product not labeled as organic.] , aloe barbadensis leaf extract, tocopheryl acetate, polysorbate 20, decyl glucoside, gluconolactone, potassium sorbate, sodium benzoate, citric acid, caprylyl/capryl glucoside, citrus reticulata (mandarin orange) peel oil, citrus aurantium dulcis (orange) peel oil, citrus grandis (grapefruit) peel oil, glycine soja oil, triethyl citrate, tocopherol

Dist. by KAS Direct, LLC
1525 Howe St., Racine, WI 53403

PRINCIPAL DISPLAY PANEL - 20 Wipe Bag Label

20
wipes

babyganics®

alcohol-free
hand sanitizing wipes

mandarin

kills 99.9% of bacteria*

dermatologist tested

Discover which of our ingredients
are certified organic on the back panel.